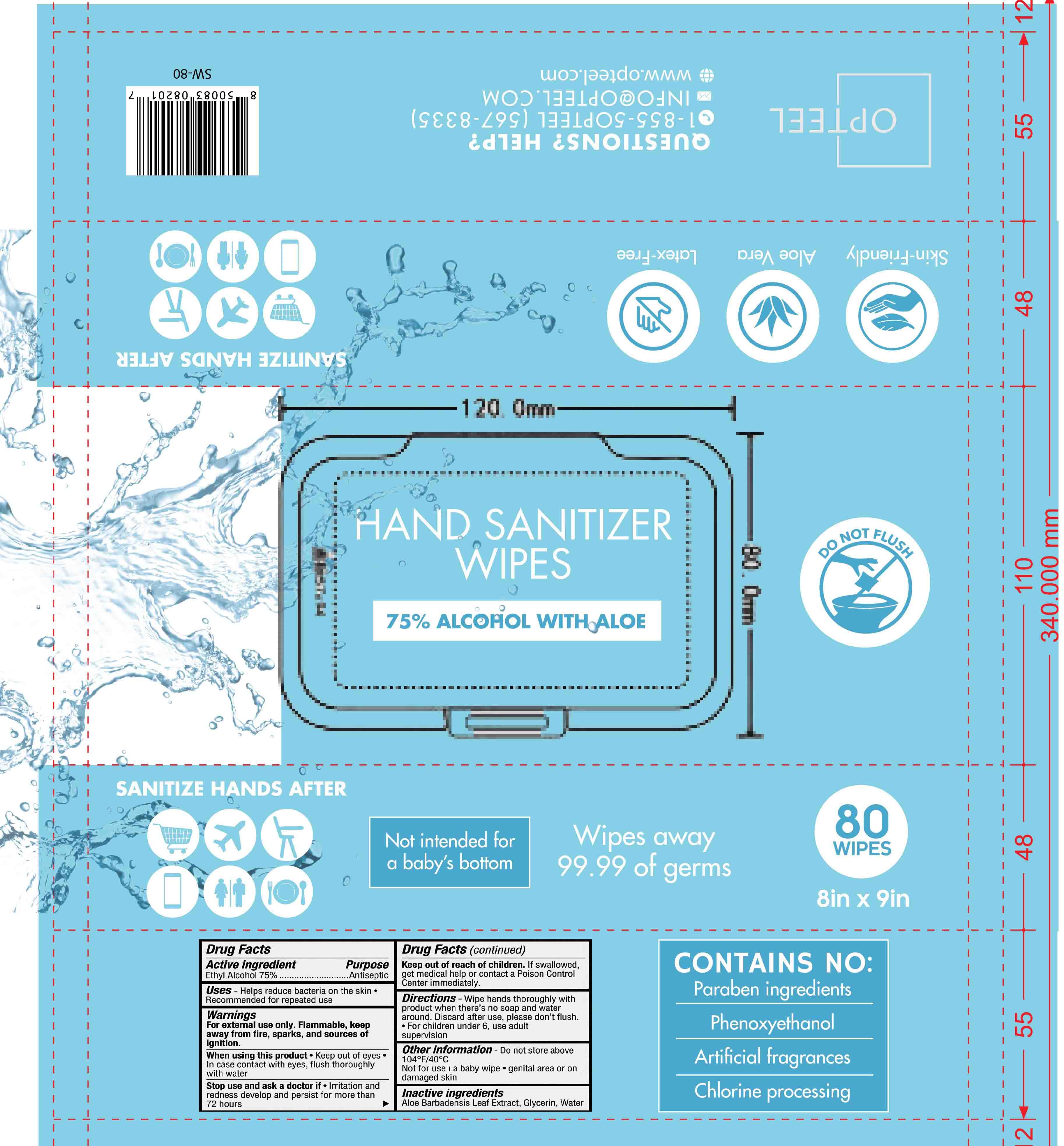 DRUG LABEL: HAND SANITIZER WIPES
NDC: 75428-035 | Form: CLOTH
Manufacturer: Shandong Baihe Sanitary Products Co., Ltd.
Category: otc | Type: HUMAN OTC DRUG LABEL
Date: 20260129

ACTIVE INGREDIENTS: ALCOHOL 75 g/100 1
INACTIVE INGREDIENTS: ALOE BARBADENSIS LEAF; GLYCERIN; WATER

75428-035-01
HAND SANITIZER WIPES

Active Ingredient (s)

Ethyl Alcohol 75%

Purpose

Antiseptic

Use

Helps reduce bacteria on the skin.Recommended for repeated use.

Warnings

For external use only.Flammable,keep away from fire,sparks,and sources of ignition.

Do not use

Do not store above 104°F/40°C。Not for use as baby wipe * genital area or on damaged skin

WHEN USING

Keep out of eyes.In case contact with eyes,flush thoroughly with water.

STOP USE

Irritation and redness develop and persist for more than 72 hours.

ASK DOCTOR

You are allergic to alcohol or any other ingredients in this product.

You have sensitive skin that is prone to irritation, rashes, or allergic reactions to topical products.

You are using other topical skin medications or treatments on the intended application area.

You are pregnant or breastfeeding and plan to use this product on a regular basis or over large areas of the body.

Keep out of reach of children. If swallowed,get medical help or contact a Poison Control Center immediately.

Directions

Wipe hands thoroughly with product when there's no soap and water around. Discard after use,please don't flush.For children under 6,use adult supervision

Other information

Packaging Integrity: Do not use if the package is torn, punctured, or damaged. Damaged packaging can lead to alcohol evaporation, contamination, or loss of disinfection efficacy.

Shelf Life & Expiration Date: Use only before the expiration date printed on the package. Expired products may have reduced alcohol content and may not effectively kill germs.

Flammability Warning (Reinforcement): 75% alcohol is a Class IB flammable liquid. Avoid use near sparks, static electricity, or any ignition source. Do not use while smoking.

Inactive ingredients

Aloe Barbadensis Leaf Extract,Glycerin，Water

QUESTIONS

Toll-Free Phone Number:1-855-5OPTEEL(567-8335)

Service Hours: [Insert Service Hours, e.g., Monday–Friday, 9:00 AM–5:00 PM (Time Zone)]

Visit the “Product Support” or “FAQ” page for additional information and troubleshooting tips.

Email:INFO@OPTEEL.COM

Please include the product name, lot number, and expiration date in your email for faster assistance.